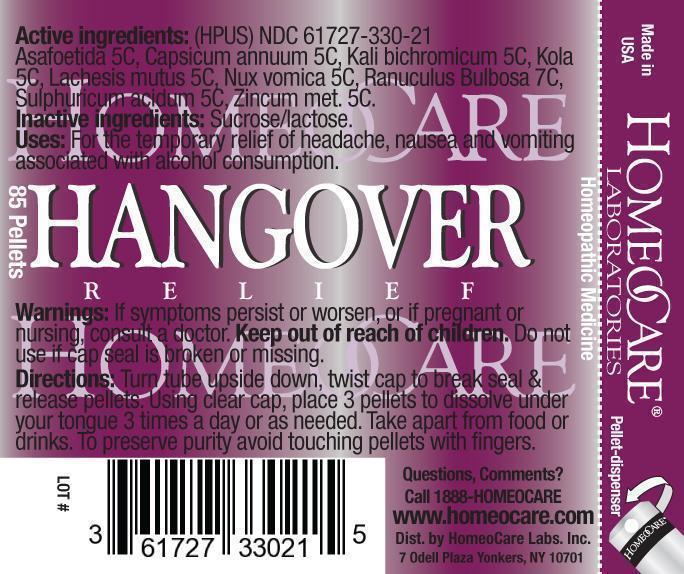 DRUG LABEL: Hangover Relief
NDC: 61727-330 | Form: PELLET
Manufacturer: Homeocare Laboratories
Category: homeopathic | Type: HUMAN OTC DRUG LABEL
Date: 20181218

ACTIVE INGREDIENTS: ASAFETIDA 5 [hp_C]/4 g; CAPSICUM 5 [hp_C]/4 g; POTASSIUM DICHROMATE 5 [hp_C]/4 g; COLA NUT 5 [hp_C]/4 g; LACHESIS MUTA VENOM 5 [hp_C]/4 g; STRYCHNOS NUX-VOMICA SEED 5 [hp_C]/4 g; RANUNCULUS BULBOSUS 7 [hp_C]/4 g; SULFURIC ACID 5 [hp_C]/4 g; ZINC 5 [hp_C]/4 g
INACTIVE INGREDIENTS: SUCROSE; LACTOSE

Hangover Relief

Active ingredients:(HPUS)

Asafoetida 5C, Capsicum annuum 5C, Kali bichromium 5C, Kola 5C, Lachesis mutus 5C, Nux vomica 5C, Ranuculus Bulbosa 7C, Sulphuricum acidum 5C, Zincum met. 5C.

Purpose:

For the temporary relief of headache, nausea and vomiting associated with alcohol consumption.

Keep out of reach of children.

Uses:

For the temporary relief of headache, nausea and vomiting associated with alcohol consumption.

Warnings:

If symptoms persist or worsen or if pregnant or nursing consult a doctor. Keep out of reach of children. Do not use if cap seal is broken or missing.

Inactive ingredients:

Sucrose/lactose.

Dosage & Administration:

Turn tube upside down, twist cap to break seal & release pellets. Using clear cap, place 3 pellets to dissolve under your tongue. 3 times a day or as needed. Take apart from food or drinks. To preserve purity avoid touching pellets with fingers.

Hangover Relief

Homeopathic Medicine

85 Pellets
hcl_label_Hangover-2012.jpg